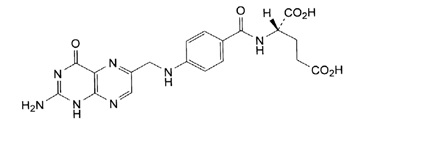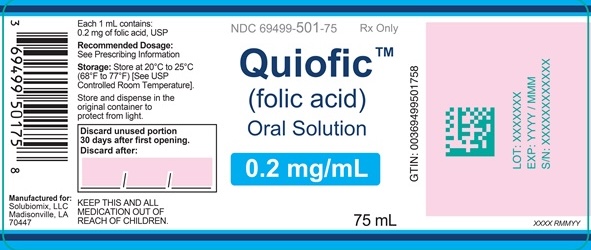 DRUG LABEL: QUIOFIC 
NDC: 69499-501 | Form: SOLUTION
Manufacturer: Solubiomix, LLC
Category: prescription | Type: HUMAN PRESCRIPTION DRUG LABEL
Date: 20260208

ACTIVE INGREDIENTS: FOLIC ACID 1 mg/5 mL
INACTIVE INGREDIENTS: SODIUM PHOSPHATE DIBASIC DIHYDRATE; SODIUM PHOSPHATE P-32, UNSPECIFIED; PROPYLENE GLYCOL; EDETATE DISODIUM; METHYLPARABEN; PROPYLPARABEN; SORBITOL SOLUTION 70%; WATER

HIGHLIGHTS OF PRESCRIBING INFORMATION

These highlights do not include all the information needed to use QUIOFIC safely and effectively. See full prescribing information for QUIOFIC.
QUIOFICTM (folic acid) oral solution
Initial U.S. Approval: 1947

1 INDICATIONS AND USAGE

QUIOFIC is a folate analog indicated for the treatment of megaloblastic anemias due to folic acid deficiency in adult and pediatric patients. (1)

2 DOSAGE AND ADMINISTRATION

- Recommended starting dosage in adults and pediatric patients (regardless of age) is up to 1 mg orally daily. (2)

- Maintenance dosage (2)

- Pediatric patients birth to 23 months: 0.1 mg orally daily

- Pediatric patients 2 years to less than 4 years: up to 0.3 mg orally daily

- Adults and pediatric patients 4 years and older: 0.4 mg orally daily

- Pregnant and Lactating Women: 0.8 mg orally daily; but never less than 0.1 mg orally per day

3 DOSAGE FORMS AND STRENGTHS

Oral Solution: 0.2 mg/mL(3)

4 CONTRAINDICATIONS

QUIOFIC is contraindicated in patients with a history of a hypersensitivity reaction to folic acid or any of the ingredients of QUIOFIC. (4)

5 WARNINGS AND PRECAUTIONS

- Folic acid in doses above 0.1 mg daily may obscure pernicious anemia in that hematologic remission can occur while neurologic manifestations remain progressive. This may result in severe nervous system damage before the correct diagnosis is made. (5.1)

6 ADVERSE REACTIONS

The most common adverse reactions are nausea, anorexia, and bloating. (6)

To report SUSPECTED ADVERSE REACTIONS, contact Solubiomix, LLC at 1-844-551-9911 or FDA at 1-800-FDA-1088 or www.fda.gov/medwatch.

7 DRUG INTERACTIONS

- Anticonvulsant action of phenytoin is antagonized by folic acid. (7)
- Multiple drug classes, including anticonvulsants, antibiotic/antimicrobial agents, folate antagonists, GI-binding agents, and oral contraceptives, may reduce folic acid absorption or folate levels. (7)

FULL PRESCRIBING INFORMATION

1 INDICATIONS AND USAGE

QUIOFIC is indicated for the treatment of megaloblastic anemias due to folic acid deficiency in adult and pediatric patients.

2 DOSAGE AND ADMINISTRATION

2.1 Important Administration Information

Instruct patients or caregivers to use an oral dosing syringe to correctly measure the prescribed amount of medication. Inform patients that oral dosing syringes may be obtained from their pharmacy.

2.2 Recommended Dosing

Initial Dosing

The recommended starting dosage of QUIOFIC in pediatric and adult patients is up to 1 mg orally daily. QUIOFIC can be taken with or without food. Rule out pernicious anemia prior to use of any doses greater than 0.4 mg (except during pregnancy and lactation).

Maintenance Dosing

When clinical symptoms have subsided and the blood picture has become normal, use a daily maintenance level as follows:
- Pediatric patients aged birth to 23 months: 0.1 mg orally daily
- Pediatric patients aged 2 years to less than 4 years: up to 0.3 mg orally daily
- Pediatric patients aged 4 years and older and adult patients: 0.4 mg orally daily
- Pregnant and Lactating Women: 0.8 mg orally daily; but never less than 0.1 mg orally per day
Higher maintenance doses may be needed in the presence of alcoholism, hemolytic anemia, anticonvulsant therapy, or chronic infection.
Monitor patients frequently for relapse and adjust dose accordingly.

3 DOSAGE FORMS AND STRENGTHS

Oral Solution: 0.2 mg/mL; yellow solution with a mixed berry flavor.

4 CONTRAINDICATIONS

QUIOFIC is contraindicated in patients with a history of a hypersensitivity reaction to folic acid or any of the ingredients of QUIOFIC [see Description (11)].

5 WARNINGS AND PRECAUTIONS

5.1 Risk of Obscuring Diagnosis of Pernicious Anemia

The use of single-agent QUIOFIC (without the use of vitamin B12) is not recommended for the treatment of pernicious anemia and other megaloblastic anemias in which vitamin B12 is deficient.
Folic acid in doses above 0.1 mg daily may obscure pernicious anemia in that hematologic remission can occur while neurologic manifestations remain progressive. There is a potential danger in administering folic acid to patients with undiagnosed anemia, since folic acid may obscure the diagnosis of pernicious anemia by alleviating the hematologic manifestations of the disease while allowing the neurologic complications to progress. This may result in severe nervous system damage before the correct diagnosis is made. Adequate doses of vitamin B12 may prevent, halt, or improve the neurologic changes caused by pernicious anemia.

6 ADVERSE REACTIONS

The following clinically significant adverse reactions are described elsewhere in the labeling:

- Risk of Obscuring Diagnosis of Pernicious Anemia [see Warnings and Precautions (5.1)]

The following adverse reactions associated with the use of folic acid were identified in clinical studies or post marketing reports. Because some of these reactions were reported voluntarily from a population of uncertain size, it is not always possible to reliably estimate their frequency or establish a causal relationship to drug exposure.
Adverse Reactions:

- Hypersensitivity reactions including rash, itching, malaise, and bronchospasm.
- Gastrointestinal reactions (nausea, anorexia, abdominal distension, flatulence, dysgeusia)
- Neurological reactions (altered sleep patterns, difficulty concentrating, irritability, overactivity, excitement, depression, confusion, impaired judgement)
- Decreased vitamin B12 serum levels (with prolonged folic acid therapy).
- Increased seizures in patients with epilepsy receiving phenobarbital, primidone, or diphenylhydantoin

7 DRUG INTERACTIONS

7.1 Impact of Folic Acid on Other Drugs

Folic acid may interfere with gastrointestinal absorption of methotrexate. Folic acid therapy in folate-deficient individuals may decrease serum levels of phenytoin. Folic acid may also interfere with the absorption and effectiveness of antibiotic tetracycline.

Folic acid supplements are usually avoided on the day of oral methotrexate administration. Generally, the time of administration of these drugs should be separated from folic acid.

7.2 Impact of Other Drugs on Folic Acid

A wide range of medications can affect folic acid levels through multiple mechanisms, including impaired absorption, accelerated metabolism, and direct inhibition of folate pathways. Enzyme-inducing anticonvulsants such as phenytoin, primidone, carbamazepine, phenobarbital, and the broader anticonvulsant class increase hepatic folate metabolism, inhibit intestinal folate-processing enzymes, raise gastrointestinal pH, or displace folate from serum proteins, collectively leading to decreased folate availability. Valproate and sulfasalazine primarily reduce intestinal folate absorption or interfere with folate-dependent metabolic pathways, while isoniazid and cycloserine reduce folate utilization through metabolic disruption. Several antifolate agents, including trimethoprim, pyrimethamine, methotrexate, and triamterene, directly inhibit dihydrofolate reductase, decreasing the formation of active folate derivatives. Additional agents such as pentamidine, antacids, cholestyramine, colestipol, and H 2 blockers impair gastrointestinal folate uptake through pH elevation, transporter inhibition, or binding of dietary folate. Nitrous oxide indirectly decreases folate activity by inactivating vitamin B12 and downstream methylation pathways, while oral contraceptives increase folate turnover and urinary loss.

While on QUIOFIC treatment, if patients are concomitantly using any of the drugs or drug classes mentioned above, then monitor for reduced efficacy and adjust the dose of QUIOFIC as needed.

8 USE IN SPECIFIC POPULATIONS

8.1 Pregnancy

Risk Summary
Available data from published studies over decades of use of folic acid in pregnant women have not identified a drug-associated risk of major birth defects, miscarriage, or adverse maternal or fetal outcomes. Pregnant women should follow the U.S. Recommended Daily Allowances for pregnancy because their folic acid requirements may exceed those of nonpregnant women. Pregnant women with folic acid deficiency during the first trimester are at increased risk of neural tube defects in the developing fetus. Animal studies to evaluate the potential reproductive and developmental toxicity have not been conducted.
The background risk of major birth defects and miscarriage for the indicated population(s) is unknown. All pregnancies have a background risk of birth defect, loss, or other adverse outcomes. In the U.S. general population, the estimated background risk of major birth defects and miscarriage in clinically recognized pregnancies is 2 to 4% and 15 to 20%, respectively.

8.2 Lactation

Risk Summary
Available data from published studies over decades of use of folic acid supplementation in lactating women have found that folic acid is present in human milk. Lactating women should follow the U.S. Recommended Dietary Allowances for their condition, because their folic acid requirements may exceed those of nonlactating women. At recommended supplementation doses, there have been no reports of adverse events in breastfed infants over decades of use. There are no data regarding the effect of folic acid on milk production. The developmental and health benefits of breastfeeding should be considered along with the mother’s clinical need for folic acid and any potential adverse effects on the breastfed child from supplemental folic acid or from the underlying maternal condition.

8.4 Pediatric Use

QUIOFIC is approved for treatment of megaloblastic anemias due to folic acid deficiency in pediatric patients [see Dosage and Administration (2)].

10 OVERDOSAGE

Consider contacting the Poison Help line (1-800-222-1222) or a medical toxicologist for additional overdose management recommendations.

11 DESCRIPTION

Folic acid, N-[p-[[(2-amino-4- hydroxy-6-pteridinyl) methyl]- amino] benzoyl]-L glutamic acid, is a B complex vitamin containing a pteridine moiety linked by a methylene bridge to para-aminobenzoic acid, which is joined by a peptide linkage to glutamic acid. Conjugates of folic acid are present in a wide variety of foods, particularly liver, kidneys, yeast, and leafy green vegetables. Commercially available folic acid is prepared synthetically. Folic acid, USP occurs as a yellow or yellowish-orange crystalline powder and is very slightly soluble in water and insoluble in alcohol. Folic acid, USP is readily soluble in dilute solutions of alkali hydroxides and carbonates, and solutions of the drug may be prepared with the aid of sodium hydroxide or sodium carbonate, thereby forming the soluble sodium salt of folic acid (sodium folate). Aqueous solutions of folic acid are heat sensitive and rapidly decompose in the presence of light and/or riboflavin; solutions should be stored in a cool place protected from light.
The structural formula of folic acid is as follows:

C19H19N7O6

M.W. 441.40

Each 1 mL of solution, for oral administration, contains 0.2 mg folic acid, USP.
QUIOFIC® (folic acid) Oral Solution, 0.2 mg/mL contains the following inactive ingredients: edetate disodium, methylparaben, mixed berry flavor, propylene glycol, propylparaben, purified water, sodium phosphate dibasic, sodium phosphate monobasic, and sorbitol solution.

12 CLINICAL PHARMACOLOGY

12.1 Mechanism of Action

Folic acid acts on megaloblastic bone marrow to produce a normoblastic marrow.
In man, an exogenous source of folate is required for nucleoprotein synthesis and the maintenance of normal erythropoiesis. Folic acid is the precursor of tetrahydrofolic acid, which is involved as a cofactor for transformylation reactions in the biosynthesis of purines and thymidylates of nucleic acids. Impairment of thymidylate synthesis in patients with folic acid deficiency is thought to account for the defective deoxyribonucleic acid (DNA) synthesis that leads to megaloblast formation and megaloblastic and macrocytic anemias.

12.2 Pharmacodynamics

Folic acid supplementation restores tetrahydrofolate-dependent activity, with reticulocytosis in 2–5 days and hematologic normalisation within 1–2 weeks. Serum folate reflects recent intake, red blood cell folate reflects long-term stores, and plasma homocysteine serves as a functional biomarker.

12.3 Pharmacokinetics

Absorption
Folic acid is absorbed from the small intestine, primarily from the proximal portion. Folic acid appears in the plasma approximately 15 to 30 minutes after an oral dose; peak levels are generally reached within 1 hour.

Distribution
Folic acid as well as its physiologically active metabolite, L-5-methyl tetrahydro folate (L-5-MTHF), can be bound to plasma proteins when entering the systemic circulation. The fraction of folic acid bound to plasma proteins, particularly albumin, ranges between ~50% to 64%. The volume of distribution of L-5-MTHF is estimated to be 32.0 L. Tetrahydrofolic acid derivatives are distributed to all body tissues but are stored primarily in the liver. Cerebrospinal fluid levels of folic acid are several times greater than serum levels of the drug.

Metabolism
The first step in the metabolism of folic acid is its reduction to dihydrofolate via dihydrofolate reductase. Subsequently, dihydrofolate is further reduced to tetrahydrofolate (THF). THF is further converted to methylene-THF by serine-hydroxymethyltransferase and reduced to physiologically active L-5-MTHF via methylenetetrahydrofolate reductase (MTHFR).

Elimination
After intravenous administration, folic acid is rapidly cleared from the plasma. Following oral administration, majority of the dose was recovered in the urine. A majority of the metabolic products appeared in the urine after 6 hours; excretion was generally complete within 24 hours. Small amounts of orally administered folic acid have also been recovered in the feces.

13 NONCLINICAL TOXICOLOGY

13.1 Carcinogenesis, Mutagenesis, Impairment of Fertility

Long-term studies in animals to evaluate carcinogenic potential and studies to evaluate the mutagenic potential or effect on fertility have not been conducted.

16 HOW SUPPLIED/STORAGE AND HANDLING

QUIOFIC (folic acid) Oral Solution, 0.2 mg/mL is a yellow solution with a mixed berry flavor supplied in amber PET bottles with a child-resistant closure containing 75 mL of oral solution (NDC 69499-501-75).

Store at 20°C to 25°C (68°F to 77°F) [see USP Controlled Room Temperature].

Store and dispense in the original container to protect from light.

Discard unused portion 30 days after first opening.

17 PATIENT COUNSELING INFORMATION

Physicians should advise patients and caregivers about the following for safe use of QUIOFIC:

- Advise patients to report signs or symptoms of hypersensitivity reaction [see Contraindications (4)].
- Instruct patients and caregivers to use an oral dosing syringe to correctly measure the prescribed amount of medication.
- Inform patients that oral dosing syringes may be obtained from their pharmacy.

Manufactured for: Solubiomix, LLC
Madisonville, LA 70447

3107 R0126

Q

NDC 69499-501-75

Rx Only

QUIOFICTM
(folic acid)
Oral Solution

0.2 mg/mL

75 mL